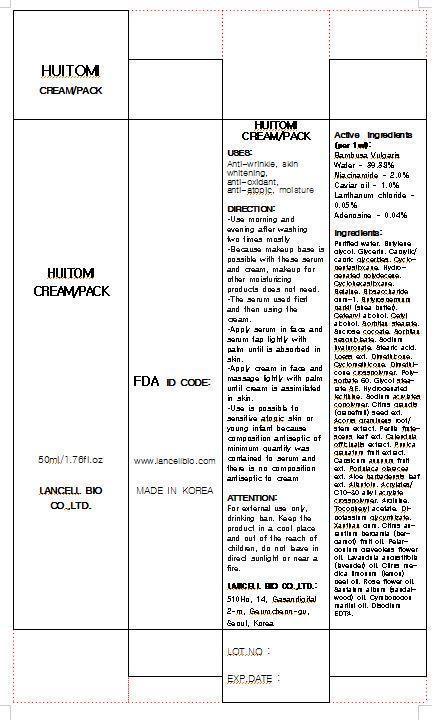 DRUG LABEL: HUITOMI PACK
NDC: 69388-6001 | Form: CREAM
Manufacturer: Lancell Bio Co., Ltd.
Category: otc | Type: HUMAN OTC DRUG LABEL
Date: 20150520

ACTIVE INGREDIENTS: GLYCERIN 5 g/100 mL
INACTIVE INGREDIENTS: WATER; NIACINAMIDE; ADENOSINE

Drug Facts

ACTIVE INGREDIENT

glycerine

INACTIVE INGREDIENT

■Purified water ■Butylene glycol ■Glycerin ■Caprylic/capric glycerides ■Cyclopentasiloxane ■Hydrogenated polydecene ■Cyclohexasiloxane ■Betaine ■Biosaccharide gum-1 ■Butyrospermum parkii (shea butter) ■Cetearyl alcohol ■Cetyl alcohol ■Sorbitan stearate ■Sucrose cocoate ■Sorbitan sesquioleate ■Sodium hyaluronate ■Stearic acid ■Loess extract ■Dimethicone ■Cyclomethicone ■Dimethicone crosspolymer ■Polysorbate 60 ■Glycol stearate SE ■Hydrogenated lecithine ■Sodium acrylates copolymer ■Citrus grandis (grapefruit) seed extract ■Acorus gramineus root/stem extract ■Perilla frutescens leaf extract ■Calendula officinalis extract ■Punica granatum fruit extract ■Capsicum annuum fruit extract ■Portulaca oleracea extract ■Aloe barbadensis leaf extract ■Allantoin ■Acrylates/C10-30 alkyl acrylate crosspolymer ■Arginine ■Tocopheryl acetate ■Dipotassium glycyrrhizate ■Xanthan gum ■Citrus aurantium bergamia (bergamot) fruit oil ■Pelargonium graveolens flower oil ■Lavandula angustifolia (lavender) oil ■Citrus medica limonum (lemon) peel oil ■Rose flower oil ■Santalum album (sandalwood) oil ■Cymbopogon martini oil ■Disodium EDTA

PURPOSE

anti wrinkle
skin whitening
anti oxidant
anti atopic
moisture

keep out of reach of children

INDICATIONS AND USAGE

Use morning and evening after washing two times mostly
Because makeup base is possible with these serum and cream, makeup for other moisturizing products does not need.
The serum used first and then using the cream.
Apply serum in face and serum tap lightly with palm until is absorbed in skin.
Apply cream in face and massage lightly with palm until cream is assimilated in skin.
Use is possible to atopic sensitive skin or young infant because composition antiseptic of minimum quantity was contained to serum and there is no composition antiseptic to cream

WARNINGS

For external use only, drinking ban
keep in a cool place

DOSAGE AND ADMINISTRATION

for external use only